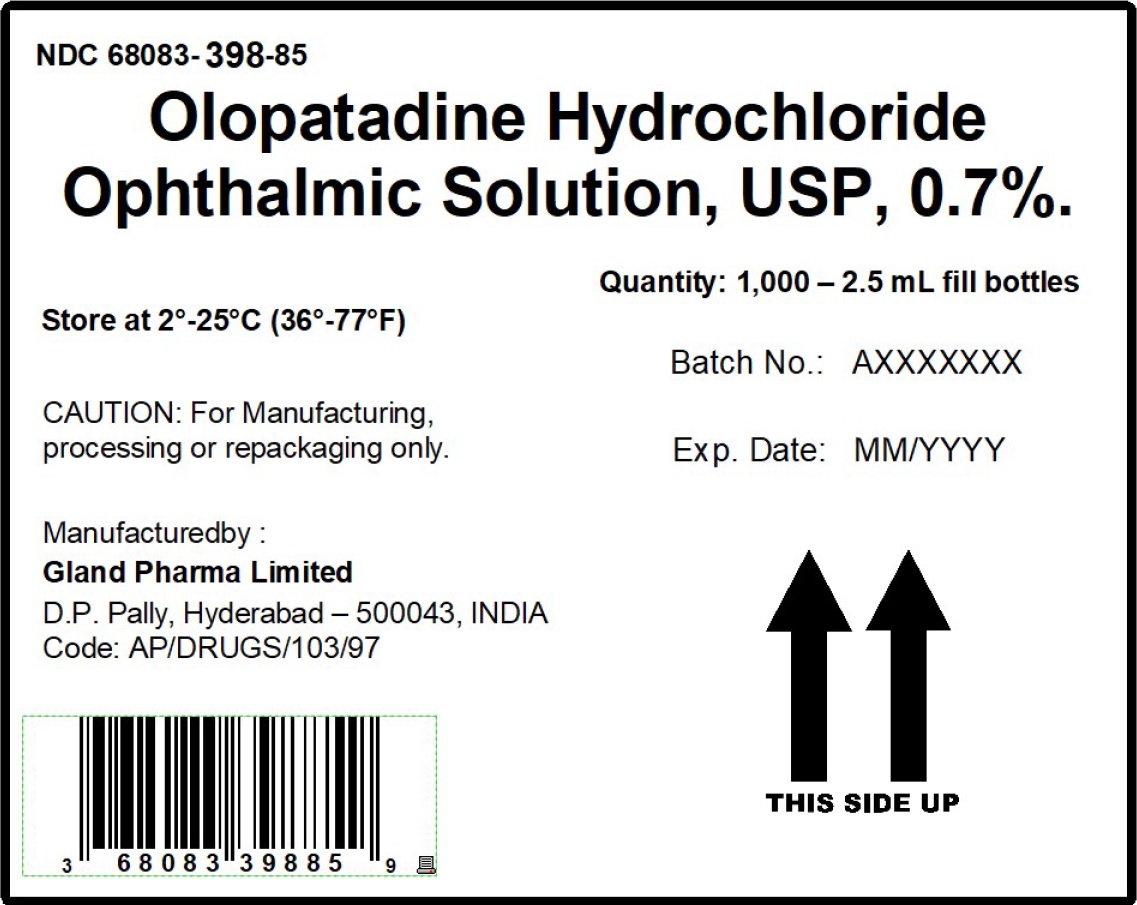 DRUG LABEL: olopatadine hydrochloride ophthalmic solution
NDC: 68083-398 | Form: SOLUTION
Manufacturer: Gland Pharma Limited
Category: other | Type: Bulk Ingredient
Date: 20260128

ACTIVE INGREDIENTS: OLOPATADINE HYDROCHLORIDE 7 mg/1 mL
INACTIVE INGREDIENTS: BENZALKONIUM CHLORIDE; BORIC ACID; HYDROCHLORIC ACID; HYDROXYPROPYL .GAMMA.-CYCLODEXTRIN; HYPROMELLOSE 2910 (4000 MPA.S); MANNITOL; POLYETHYLENE GLYCOL 400; POVIDONE K30; SODIUM HYDROXIDE; WATER

PACKAGE LABEL.PRINCIPAL DISPLAY PANEL

BULK LABEL

NDC 68083-398-85

Olopatadine Hydrochloride Ophthalmic Solution, USP, 0.7%.
Quantity- 1,000 - 2.5 mL fill Bottles

Batch No. : AXXXXXXX

Exp. Date : MM/YYYY

Store at 2°-25°C (36°-77°F)

CAUTION: For Manufacturing, processing or repackaging only.

Manufactured by :

Gland Pharma Limited

D.P. Pally, Hyderabad - 500043, INDIA

Code: AP/DRUGS/103/97